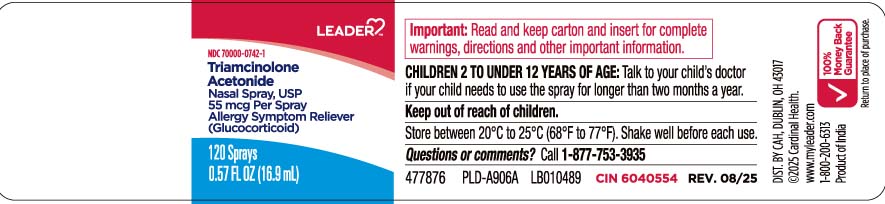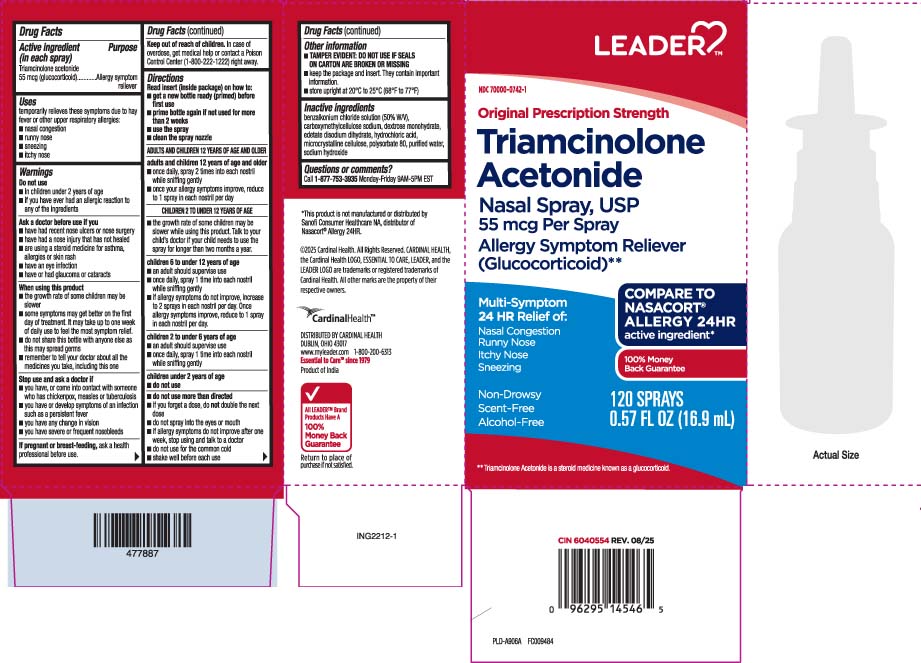 DRUG LABEL: Triamcinolone Acetonide
NDC: 70000-0742 | Form: SPRAY, METERED
Manufacturer: Cardinal Health (Leader) 70000
Category: otc | Type: HUMAN OTC DRUG LABEL
Date: 20251126

ACTIVE INGREDIENTS: TRIAMCINOLONE ACETONIDE 55 ug/1 1
INACTIVE INGREDIENTS: BENZALKONIUM CHLORIDE; DEXTROSE MONOHYDRATE; EDETATE DISODIUM; HYDROCHLORIC ACID; SODIUM HYDROXIDE; WATER; MICROCRYSTALLINE CELLULOSE; POLYSORBATE 80; CARBOXYMETHYLCELLULOSE SODIUM, UNSPECIFIED

Drug Facts

Active ingredient (in each spray)

Triamcinolone acetonide 55 mcg (glucocorticoid)

Purpose

Allergy symptom reliever

Uses

Temporarily relieves these symptoms of hay fever or other upper respiratory allergies:

- nasal congestion
- runny nose
- sneezing
- itchy nose

Warnings

Do not use

- In children under 2 years of age
- If you have ever had an allergic reaction to any of the ingredients

Ask a doctor before use if you

- have had recent nose ulcers or nose surgery
- have had a nose injury that has not healed
- are using a steroid medicine for asthma, allergies or skin rash
- have an eye infection
- have or had glaucoma or cataracts

When using this product

- the growth rate of some children may be slower
- some symptoms may get better on the first day of treatment. It may take up to one week of daily use to feel the most symptom relief.
- do not share this bottle with anyone else as this may spread germs
- remember to tell your doctor about all the medicines you take, including this one

Stop use and ask a doctor if

- you have, or come in contact with someone who has, chickenpox, measles or tuberculosis
- you have or develop symptoms of an infection such as persistent fever
- you have any change in vision
- you have severe or frequent nosebleeds

If pregnant or breast-feeding,

ask a health professional before use.

Keep out of reach of children.

In case of overdose, get medical help or contact a Poison Control Center (1800-222-1222) right away.

Directions

Read insert (*inside package) on how to:

- get a new bottle ready (primed before first use
- prime bottle again if not used for more than 2 weeks
- use the spray nozzle

ADULTS AND CHILDREN 12 YEARS OF AGE AND OLDER

adults and children 12 years of age and older

- once daily, spray 2 times into each nostril while sniffing gently
- once your allergy symptoms improve, reduce to 1 spray in each nostril per day

CHILDREN 2 TO UNDER 12 YEARS OF AGE

- the growth rate of some children may be slower while using this product. Talk to your child's doctor if your child to use the spray for longer than two months a year

children 6 to under 12 years of age

- an adult should supervise use
- once daily, spray 1 time into each nostril while sniffing gently
- if allergy symptoms do not improve, increase to 2 sprays in each nostril per day. Once allergy symptoms improve, reduce to 1 spray in each nostril per day.

children 2 to under 6 years of age

- an adult should supervise use
- once daily, spray 1 time into each nostril while sniffing gently

CHILDREN UNDER 2 YEARS OF AGE

- do not use
- do not use more than directed
- if you forget a dose, do not double the next dose
- do not spray into the eyes or mouth
- if allergy symptoms do not improve after one weeks, stop using and talk to a doctor
- do not use for the common cold
- shake well before each use

Other information

- TAMPER EVIDENT: DO NOT USE IF SEALS ON CARTON ARE BROKEN OR MISSING
- keep package and insert. They contain important information.
- Store upright 20ºC to 25ºC (68ºF to 77ºF)

Inactive ingredients

benzalkonium chloride solution (50% W/V) carboxymethylcellulose sodium, dextrose monohydrate, edetate disodium dihydrate, hydrochloric acid, microcrystalline cellulose, polysorbate 80 purified water, sodium hydroxide

Questions or comments?

Call 1-877-753-3935 Monday-Friday 9AM-5PM EST

Principal Display Panel

COMPARE TO NASACORT® ALLERGY 24HR active ingredient*

Original Prescription Strength

Triamcinolone Acetonide

Nasal Spray, USP

55 mcg per spray

Allergy Symptom Reliever

(Glucocorticoid)**

Multi-Symptom

24-HR Relief of:

Nasal Congestion

Runny Nose

Itchy Nose

Sneezing

Non-Drowsy

Scent-Free

Alcohol-Free

FL OZ (mL)

**Triamcinolone Acetonide is a steroid medicine known as a glucocorticoid.

*This product is not manufactured or distributed by Sanofi Consumer Healrhcare NA, Distributor of Nasacort® Allergy 24HR

DISTRIBUTED BY CARDINAL HEALTH

DUBLIN, OHIO 43017

Package label

LEADER Triamcinolone Acetonide Nasal Spray
LEADER Triamcinolone Acetonide Nasal Spray